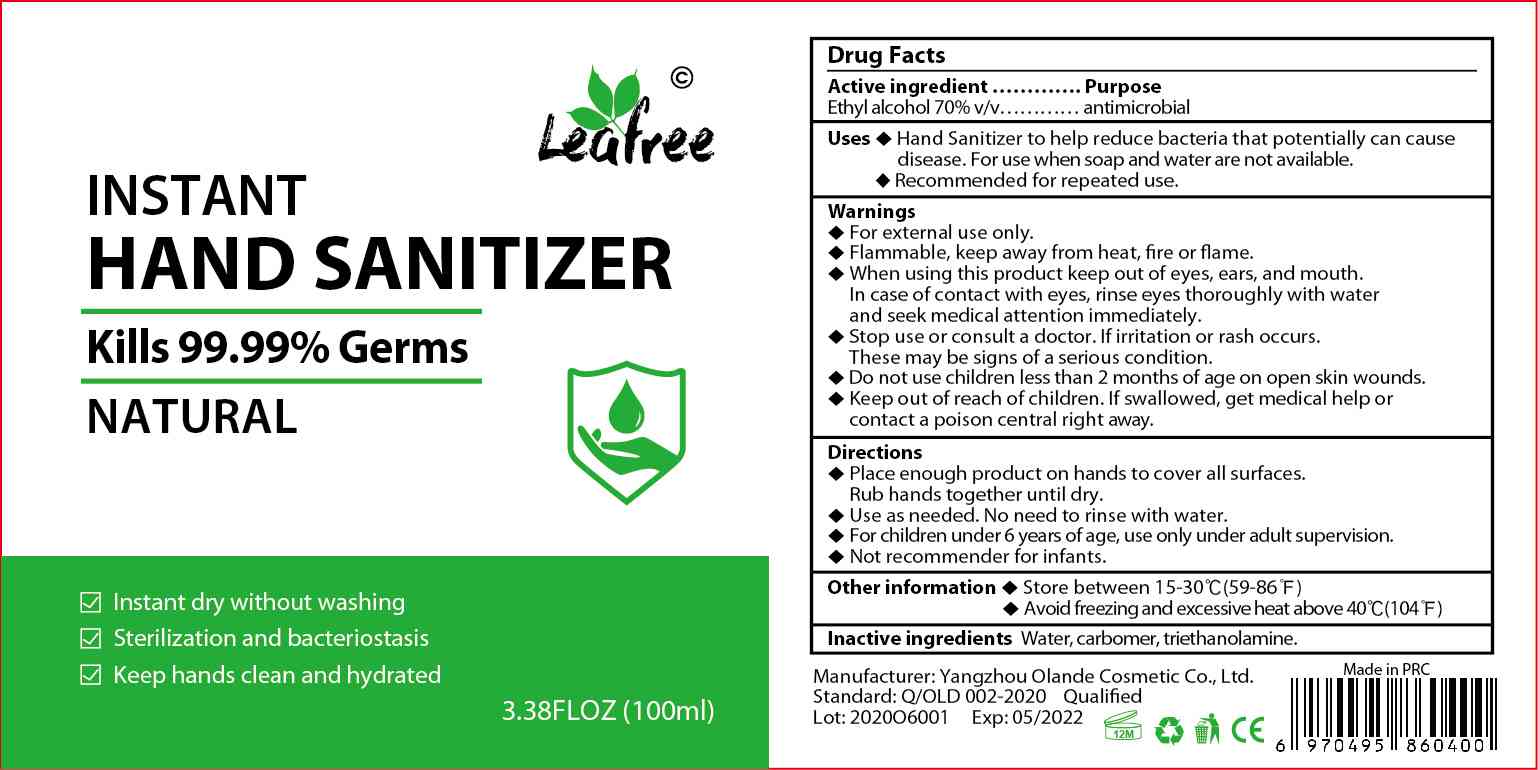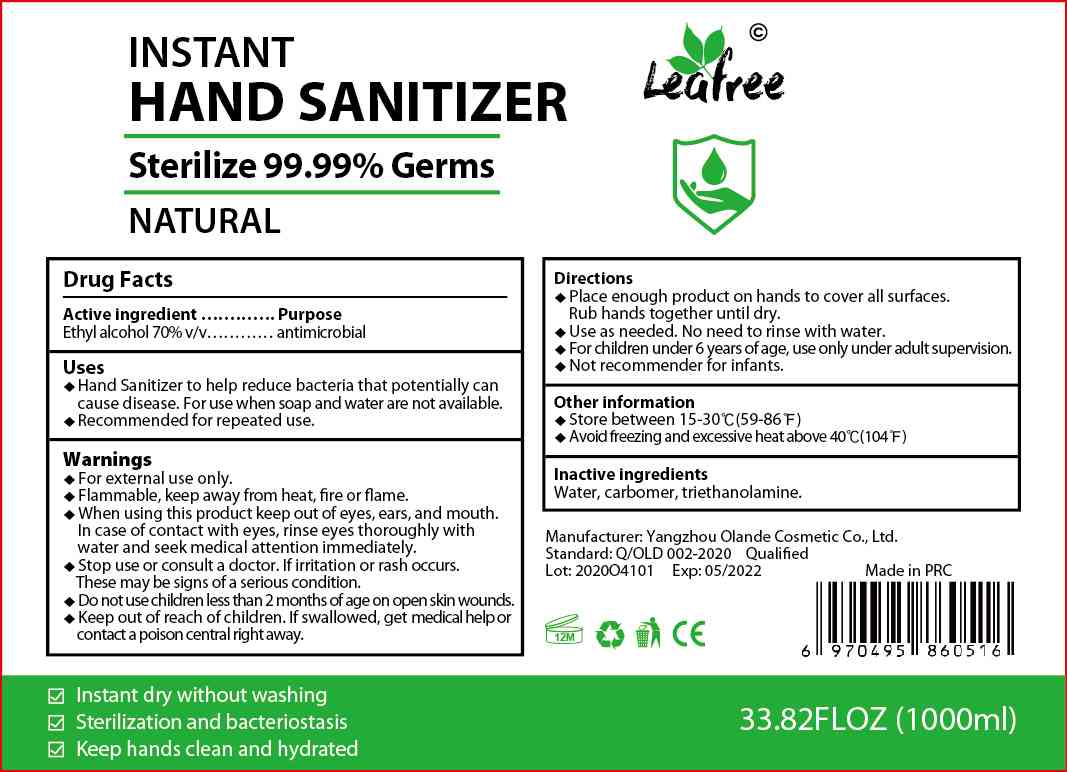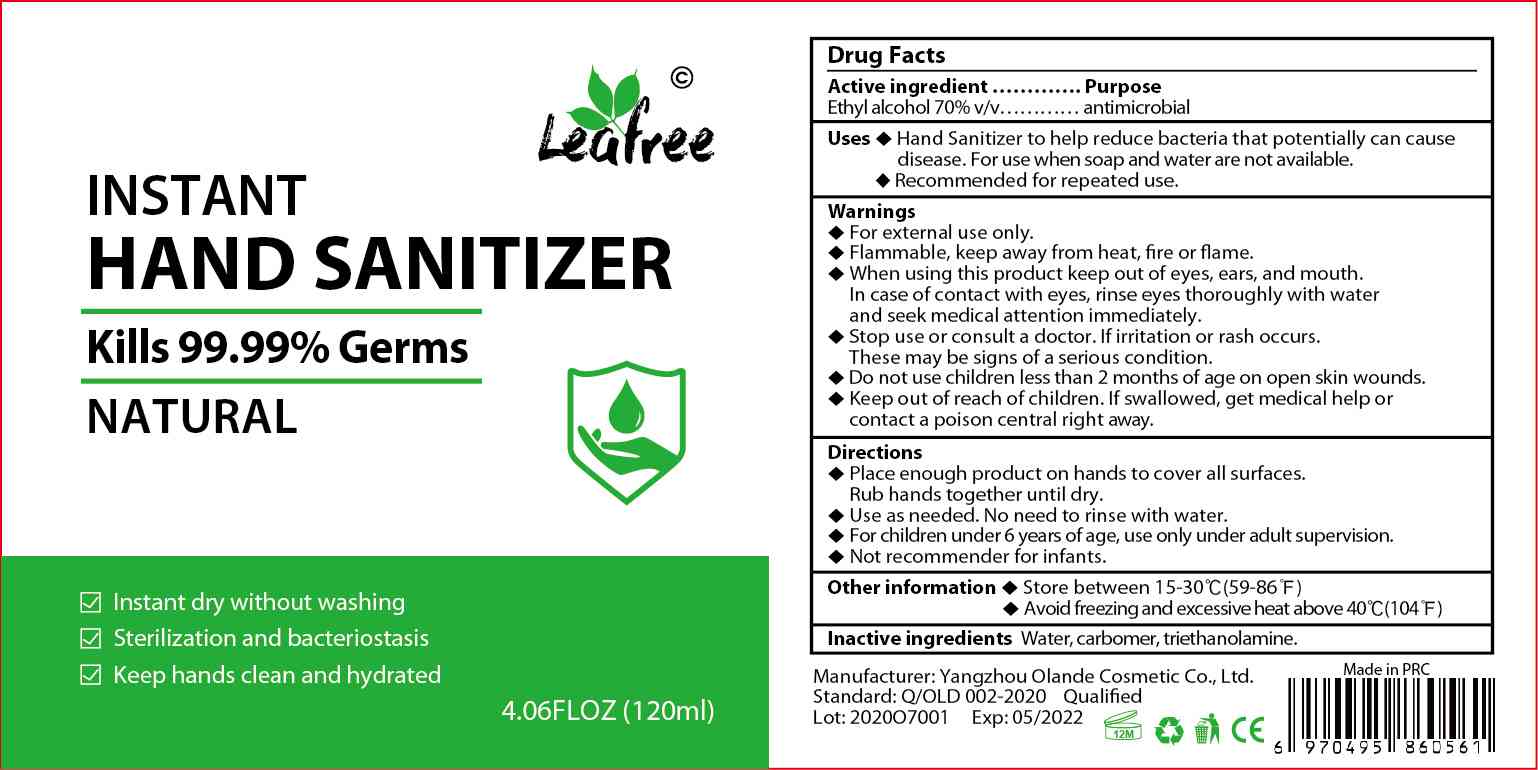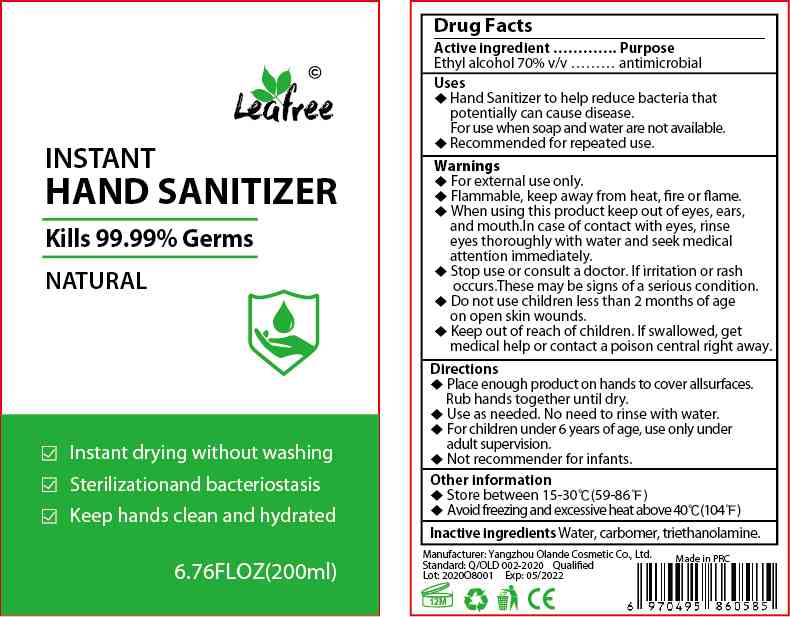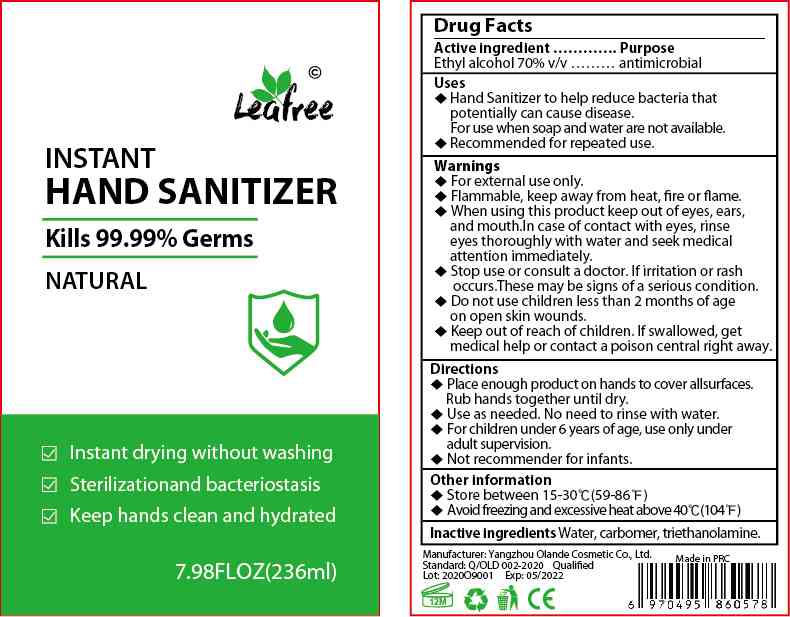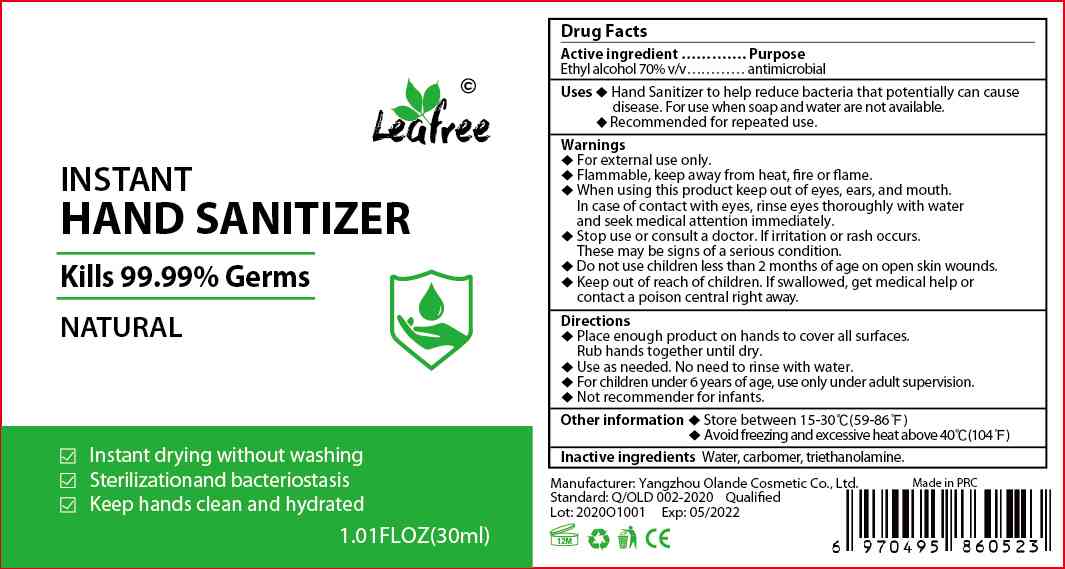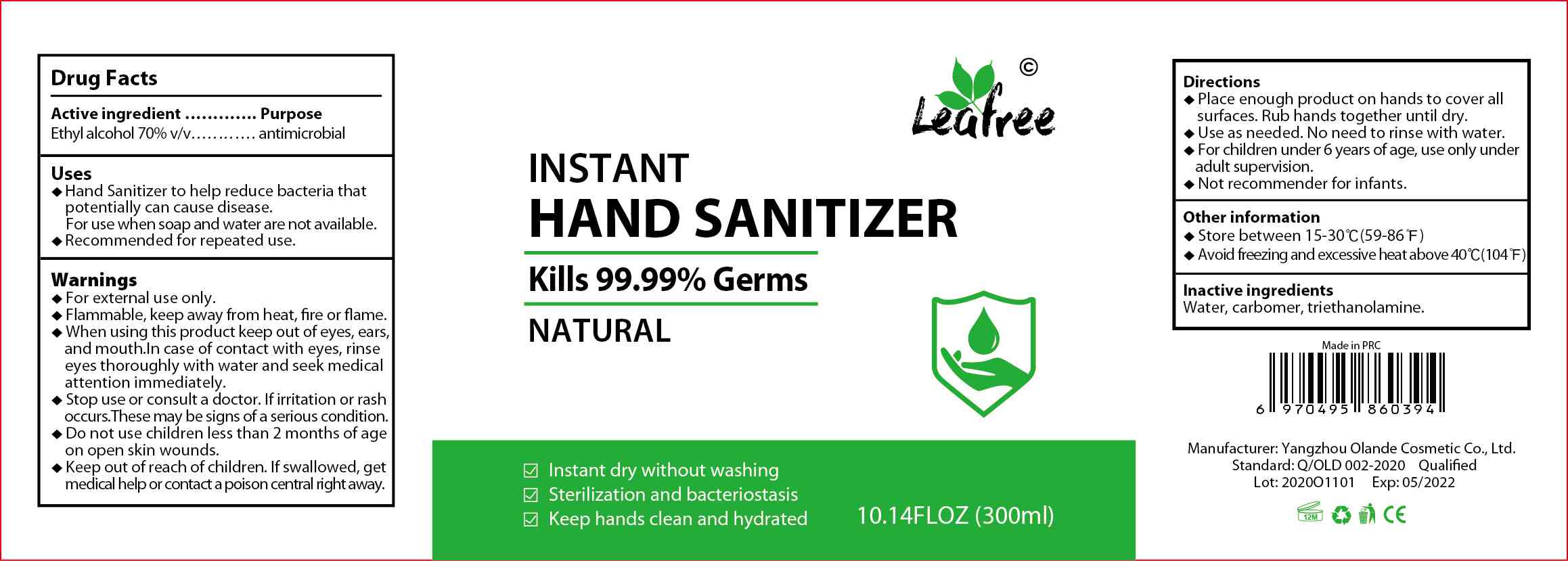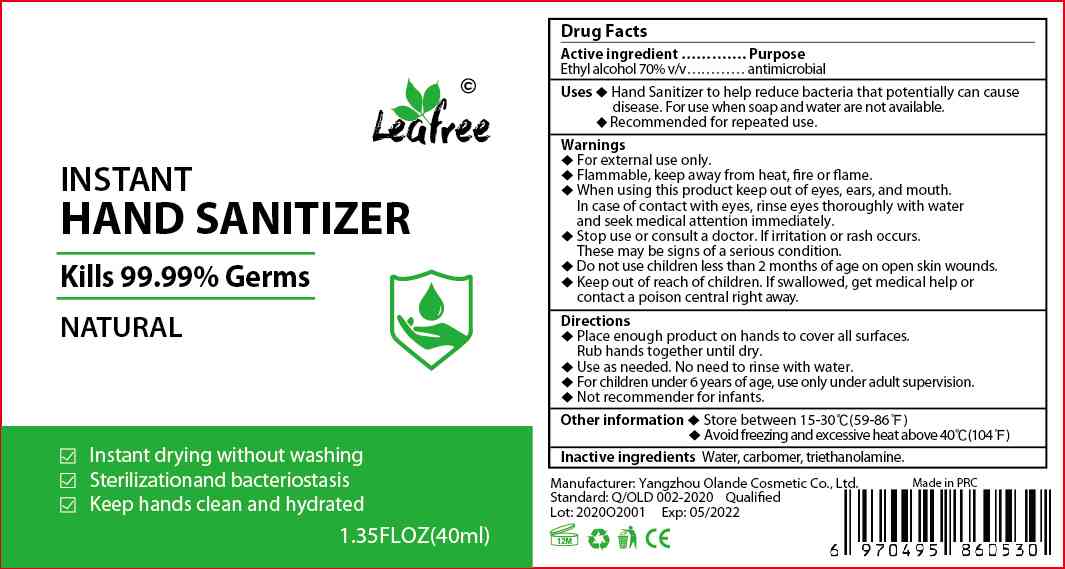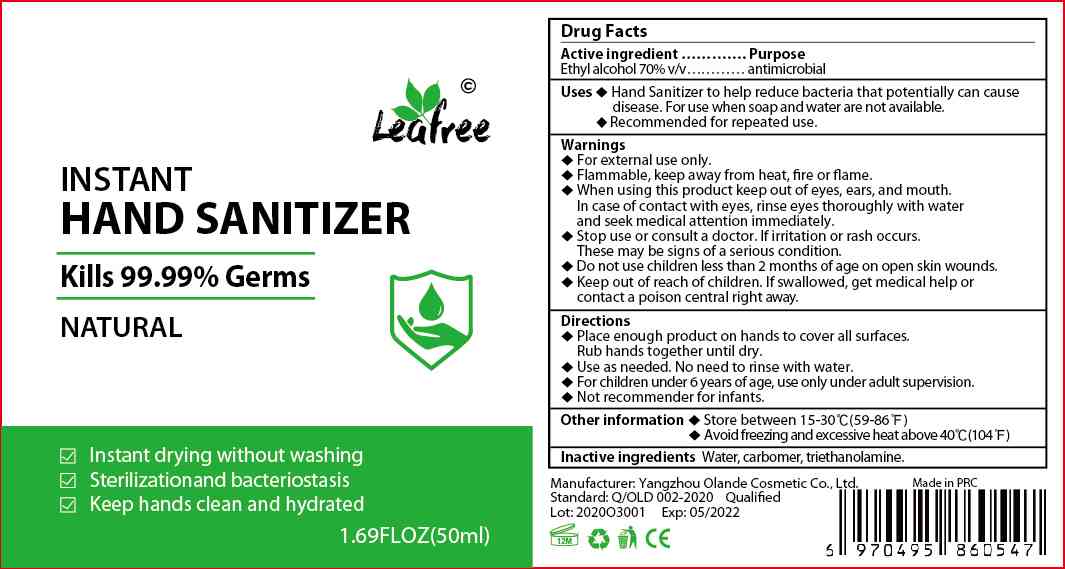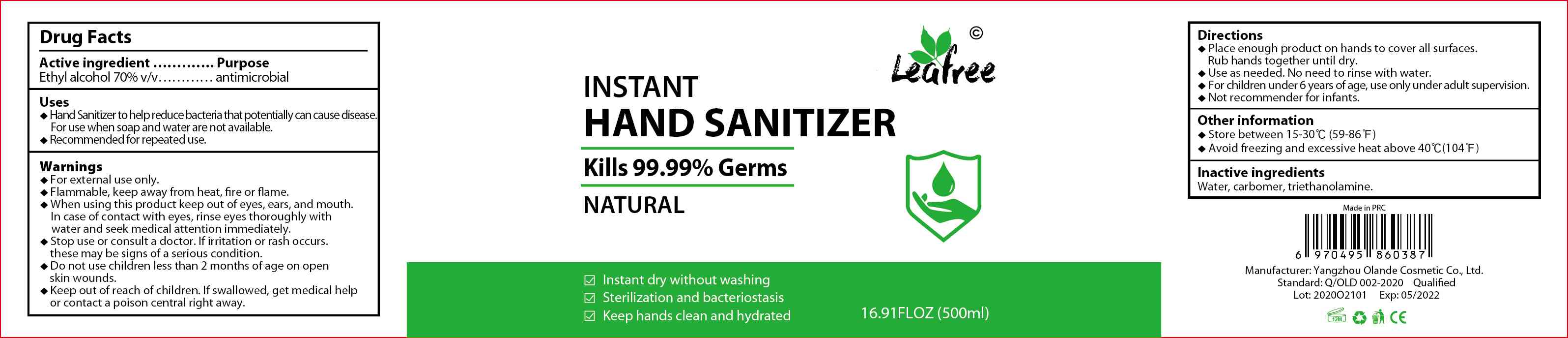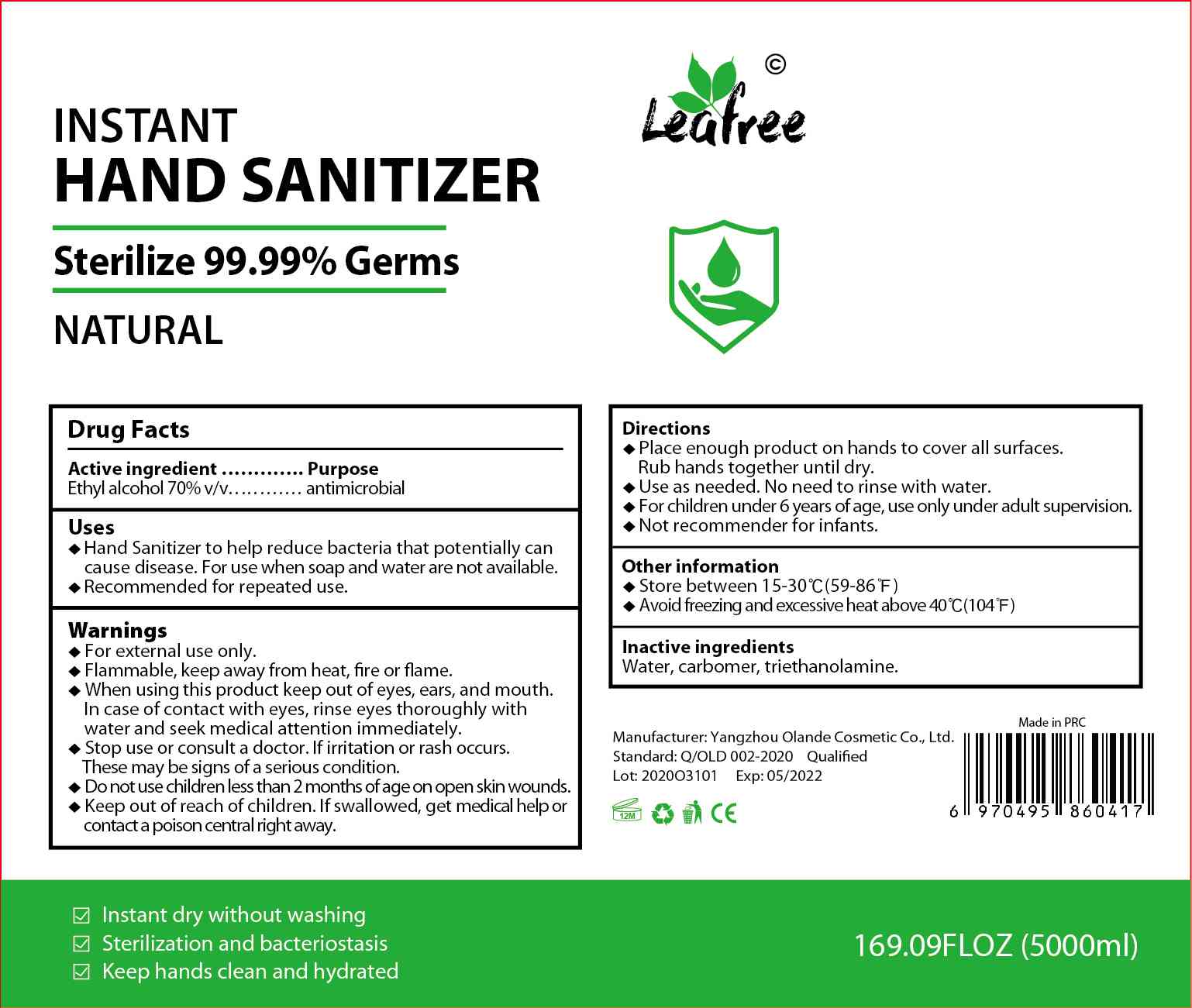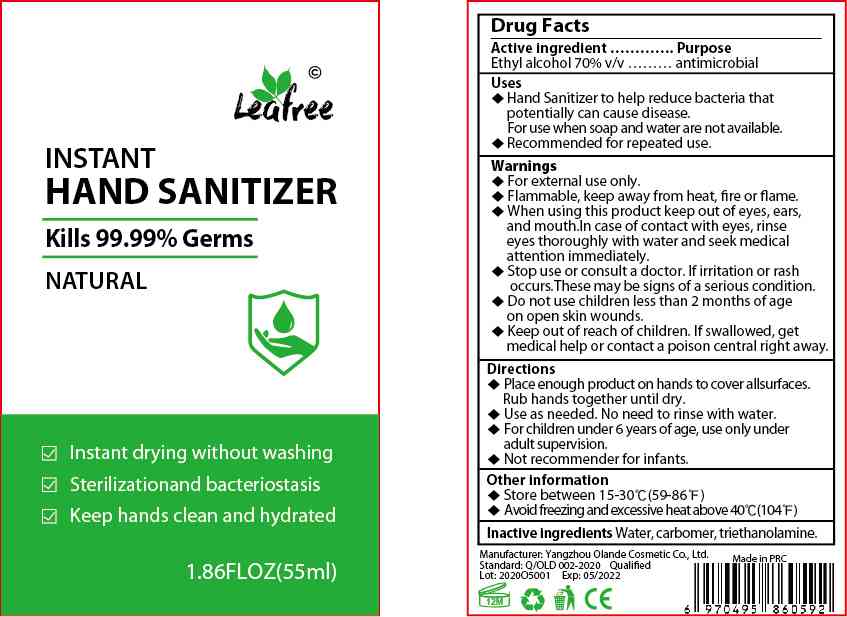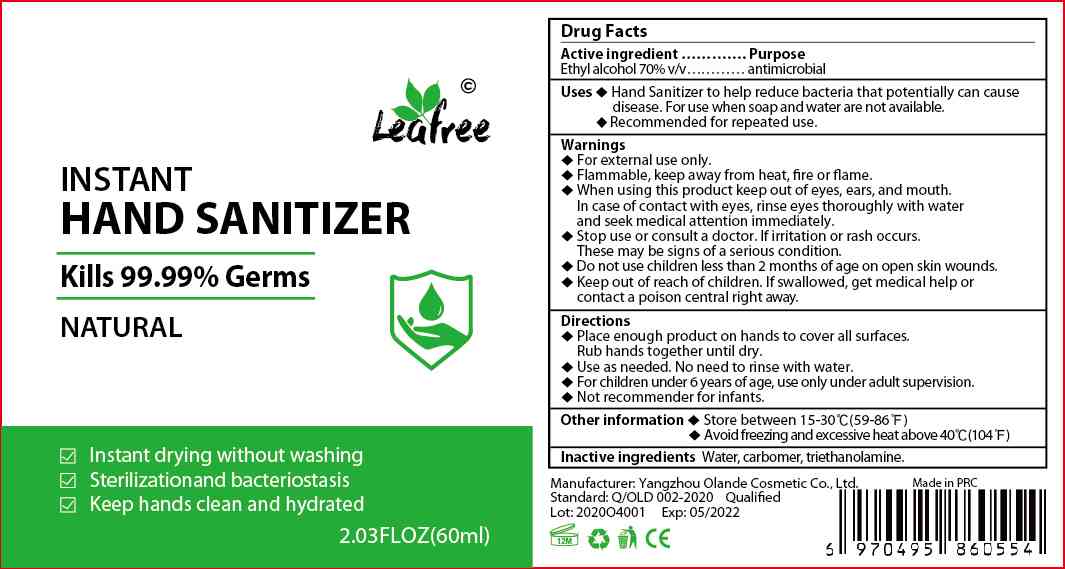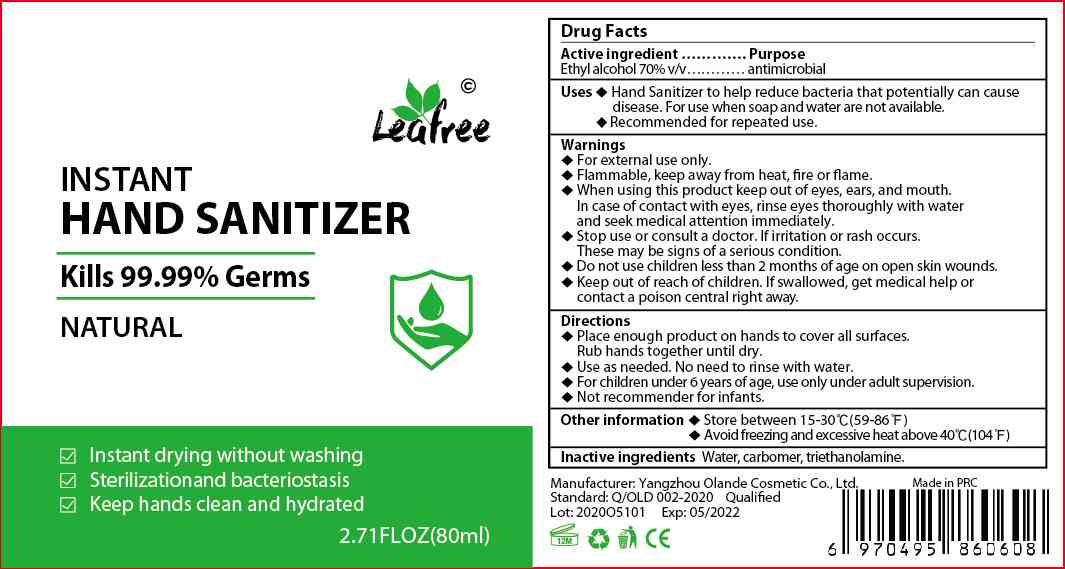 DRUG LABEL: INSTANT HAND SANITIZER
NDC: 78026-015 | Form: GEL
Manufacturer: YANGZHOU OLANDE COSMETIC CO., LTD.
Category: otc | Type: HUMAN OTC DRUG LABEL
Date: 20200602

ACTIVE INGREDIENTS: ALCOHOL 70 mL/100 mL
INACTIVE INGREDIENTS: CARBOMER HOMOPOLYMER, UNSPECIFIED TYPE; TROLAMINE; WATER

INSTANT HAND SANITIZER

Active Ingredient(s)

Ethyl alcohol 70% v/v

Purpose

antimicrobial

Use

Hand sanitizer to help reduce bacteria that potentially can cause disease. For

use when soap and water are not available.
Recommended for repeated use.

Warnings

For external use only.
Flammable keep away from heat, fire or flame.

Do not use children less than 2 months of age on open skin wounds.

When using this product keep out of eyes, ears, and mouth.
In case of contact with eyes, rinse eyes thoroughly with water and seek medical attention immediately.

Stop use or consult a doctor If irritation or rash occurs.
These may be signs of a serious condition.

Keep out of reach of children. If swallowed, get medical help or contact a Poison Control Center right away.

Directions

Place enough product on hands to cover all surfaces.
Rub hands together until dry.
Use as needed no need to rinse with water.
For children under 6 years of age, use only under adult supervision.
Not recommender for infants.

Other information

Store between 15-30°C(59-86°F)
Avoid freezing and excessive heat above 40°C(104°F)

Inactive ingredients

Water, carbomer, triethanolamine